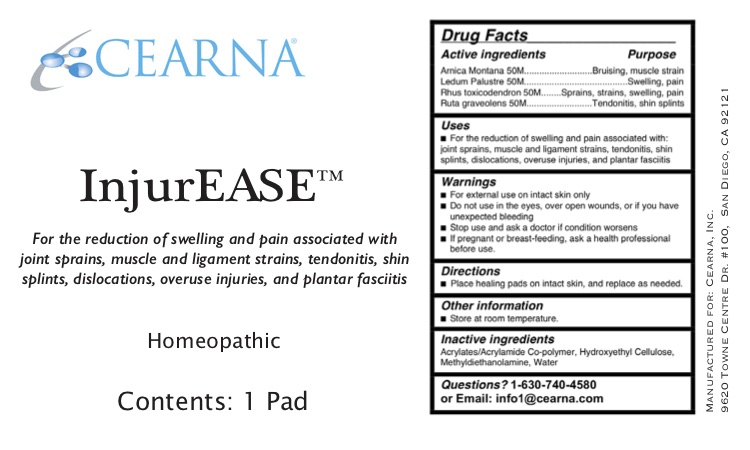 DRUG LABEL: InjurEASE
NDC: 76277-212 | Form: GEL
Manufacturer: Cearna, Inc.
Category: homeopathic | Type: HUMAN OTC DRUG LABEL
Date: 20200526

ACTIVE INGREDIENTS: ARNICA MONTANA 50 [hp_M]/1 g; TOXICODENDRON PUBESCENS LEAF 50 [hp_M]/1 g; RUTA GRAVEOLENS FLOWERING TOP 50 [hp_M]/1 g; LEDUM PALUSTRE TWIG 50 [hp_M]/1 g
INACTIVE INGREDIENTS: HYDROXYETHYL CELLULOSE, UNSPECIFIED; WATER; BUTYL ACRYLATE/METHYL METHACRYLATE/METHACRYLIC ACID COPOLYMER (18000 MW); METHYL DIETHANOLAMINE

Active Ingredients for Healing Gels:

Arnica Montana 50M

Ledum Palustre 50M

Rhus toxicodendron 50M

Ruta graveolens 50M

Purpose:

Arnica Montana 50M...........................Bruising, muscle strain

Ledum Palustre 50M.........................................Swelling, pain

Rhus toxicodendron 50M........Sprains, strains, swelling, pain

Ruta graveolens 50M..........................Tendonitis, shin splints

INDICATIONS AND USAGE

For the reduction of swelling and pain associated with: joint sprains, muscle and ligament strains, tendonitis, shin splints, dislocations, overuse injuries, and plantar fasciitis.

Warnings

- For external use on intact skin only
- Do not use in the eyes, over open wounds, or if you have unexpected bleeding
- Stop use and ask a doctor if condition worsens
- If pregnant or breast-feeding, ask a health professional before use.

Do not use:

Do not use in the eyes, over open wounds, or if you have unexpected bleeding

Stop use and ask a doctor if condition worsens

PREGNANCY OR BREAST FEEDING

I f pregnant or breast-feeding ask a health professional before use.

Keep out of reach of children.

Directions

Place healing pads on intact skin, and replace as needed

Other information

Store at room temperature.

INACTIVE INGREDIENT

Acrylates/Acrylamide Co-polymer, Hydroxyethyl Cellulose, Methyldiethanolamine, Water

Questions

Questions: 1-630-740-4580

or Email info1@cearna.com

DESCRIPTION

The letters HPUS indicate that the component(s) in this product is (are) officially monographed in the Homeopathic Pharmacopeia of the United States.

Do not use if pouches are open.